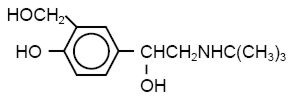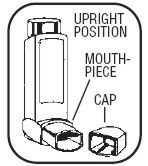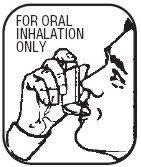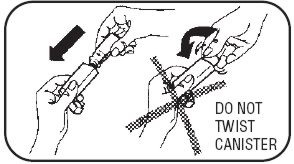 DRUG LABEL: Unknown
Manufacturer: Warrick Pharmaceuticals Corporation
Category: prescription | Type: HUMAN PRESCRIPTION DRUG LABELING
Date: 20061207

Albuterol, USP Inhalation Aerosol
Bronchodilator Aerosol
FOR ORAL INHALATION ONLY

DESCRIPTION

The active component of Albuterol Inhalation Aerosol is albuterol, USP racemic α^1-[(tert-butylamino)methyl]-4-hydroxy-m-xylene-α,α'-diol), a relatively selective beta2-adrenergic bronchodilator, having the chemical structure:

The molecular weight of albuterol is 239.3, and the empirical formula is C13H21NO3. Albuterol is a white to off-white crystalline solid. It is soluble in ethanol, sparingly soluble in water, and very soluble in chloroform. The World Health Organization recommended name for albuterol base is salbutamol.

Albuterol Inhalation Aerosol is a pressurized metered-dose aerosol unit for oral inhalation. It contains a microcrystalline suspension of albuterol in propellants (trichloromonofluoromethane and dichlorodifluoromethane) with oleic acid. Each actuation delivers 100 mcg albuterol, USP from the valve and 90 mcg of albuterol, USP from the mouthpiece. Each 17.0 g canister provides 200 oral inhalations. Each 6.8 g canister provides 80 oral inhalations.

Albuterol Inhalation Aerosol should be primed by actuating into air, away from the eyes and face, four times before using for the first time and two times when the aerosol has not been used for a period of at least four days.

CLINICAL PHARMACOLOGY

The primary action of beta-adrenergic drugs, including albuterol, is to stimulate adenyl cyclase, the enzyme which catalyzes the formation of cyclic-3',5'-adenosine monophosphate (cyclic AMP) from adenosine triphosphate (ATP) in beta-adrenergic cells. The cyclic AMP thus formed mediates the cellular responses. Increased cyclic AMP levels are associated with relaxation of bronchial smooth muscle and inhibition of release of mediators of immediate hypersensitivity from cells, especially from mast cells.

In vitro studies and in vivo pharmacologic studies have demonstrated that albuterol has a preferential effect on beta2-adrenergic receptors compared with isoproterenol. While it is recognized that beta2-adrenergic receptors are the predominant receptors in bronchial smooth muscle, data indicate that there is a population of beta2-receptors in the human heart existing in a concentration between 10% and 50%. The precise function of these receptors has not been established.

In controlled clinical trials, albuterol has been shown to have more effect on the respiratory tract, in the form of bronchial smooth muscle relaxation than isoproterenol at comparable doses while producing fewer cardiovascular effects. Controlled clinical studies and other clinical experience have shown that inhaled albuterol, like other beta-adrenergic agonist drugs, can produce a significant cardiovascular effect in some patients, as measured by pulse rate, blood pressure, symptoms, and/or ECG changes.

Albuterol is longer acting than isoproterenol in most patients by any route of administration because it is not a substrate for the cellular uptake processes for catecholamines nor for catechol-O-methyl transferase.

The effects of rising doses of albuterol and isoproterenol aerosols were studied in volunteers and asthmatic patients. Results in normal volunteers indicated that the propensity for increase in heart rate for albuterol is ½ to ¼ that of isoproterenol. In asthmatic patients similar cardiovascular differentiation between the two drugs was also seen.

Preclinical

Intravenous studies in rats with albuterol sulfate have demonstrated that albuterol crosses the blood-brain barrier and reaches brain concentrations that are amounting to approximately 5.0% of the plasma concentrations. In structures outside the blood-brain barrier (pineal and pituitary glands), albuterol concentrations were found to be 100 times those in the whole brain.

Studies in laboratory animals (minipigs, rodents, and dogs) have demonstrated the occurrence of cardiac arrhythmias and sudden death (with histologic evidence of myocardial necrosis) when beta-agonists and methylxanthines are administered concurrently. The clinical significance of these findings is unknown.

Pharmacokinetics

Because of its gradual absorption from the bronchi, systemic levels of albuterol are low after inhalation at recommended doses.

Administration of tritiated albuterol by inhalation to four subjects resulted in maximum plasma concentrations within 2 to 4 hours. Due to the insensitivity of the assay method, the metabolic rate and half-life of elimination of albuterol in plasma could not be determined. However, data from urinary excretion studies indicated that albuterol has an elimination half-life of 3.8 hours. Approximately 72% of the inhaled dose is excreted in the urine within 24 hours, 28% as unchanged drug and 44% as metabolite.

Clinical Trials

In controlled clinical trials the onset of improvement in pulmonary function was within 15 minutes, as determined by both maximal midexpiratory flow rate (MMEF) and FEV1. MMEF measurements also showed that near maximum improvement in pulmonary function generally occurs within 60 to 90 minutes, following 2 inhalations of albuterol and that clinically significant improvement generally continues for 3 to 4 hours in most patients. In clinical trials, some patients with asthma showed a therapeutic response (defined by maintaining FEV1 values 15% or more above baseline) which was still apparent at 6 hours. Continued effectiveness of albuterol was demonstrated over a 13-week period in these same trials.

In clinical studies, 2 inhalations of albuterol taken approximately 15 minutes prior to exercise prevented exercise-induced bronchospasm, as demonstrated by the maintenance of FEV1 within 80% of baseline values in the majority of patients. One of these studies also evaluated the duration of the prophylactic effect to repeated exercise challenges, which was evident at 4 hours in the majority of patients, and at 6 hours in approximately one third of the patients.

INDICATIONS AND USAGE

Albuterol Inhalation Aerosol is indicated in patients 12 years of age and older, for the prevention and relief of bronchospasm in patients with reversible obstructive airway disease, and for the prevention of exercise-induced bronchospasm.

CONTRAINDICATIONS

Albuterol Inhalation Aerosol is contraindicated in patients with a history of hypersensitivity to albuterol or any of its components.

WARNINGS

Deterioration of Asthma

Asthma may deteriorate acutely over a period of hours, or chronically over several days or longer. If the patient needs more doses of Albuterol Inhalation Aerosol than usual, this may be a marker of destabilization of asthma and requires re-evaluation of the patient and the treatment regimen, giving special consideration to the possible need for anti-inflammatory treatment, eg, corticosteroids.

Use of Anti-inflammatory Agents

The use of beta-adrenergic agonist bronchodilators alone may not be adequate to control asthma in many patients. Early consideration should be given to adding anti-inflammatory agents, eg, corticosteroids.

Paradoxical Bronchospasm

Albuterol Inhalation Aerosol can produce paradoxical bronchospasm, which may be life threatening. If paradoxical bronchospasm occurs, Albuterol Inhalation Aerosol should be discontinued immediately and alternative therapy instituted. It should be recognized that paradoxical bronchospasm, when associated with inhaled formulations, frequently occurs with the first use of a new canister or vial.

Cardiovascular Effects

Albuterol Inhalation Aerosol, like all other beta-adrenergic agonists, can produce a clinically significant cardiovascular effect in some patients as measured by pulse rate, blood pressure, and/or symptoms. Although such effects are uncommon after administration of Albuterol Inhalation Aerosol at recommended doses, if they occur, the drug may need to be discontinued. In addition, beta-agonists have been reported to produce electrocardiogram (ECG) changes, such as flattening of the T wave, prolongation of the QTc interval, and ST segment depression. The clinical significance of these findings is unknown. Therefore, Albuterol Inhalation Aerosol, like all sympathomimetic amines, should be used with caution in patients with cardiovascular disorders, especially coronary insufficiency, cardiac arrhythmias, and hypertension.

Immediate hypersensitivity reactions may occur after administration of albuterol, as demonstrated by rare cases of urticaria, angioedema, rash, bronchospasm, anaphylaxis, and oropharyngeal edema.

PRECAUTIONS

General

Albuterol, as with all sympathomimetic amines, should be used with caution in patients with cardiovascular disorders, especially coronary insufficiency, cardiac arrhythmias, and hypertension; in patients with convulsive disorders, hyperthyroidism, or diabetes mellitus; and in patients who are unusually responsive to sympathomimetic amines. Clinically significant changes in systolic and diastolic blood pressure have been seen and could be expected to occur in some patients after use of any beta-adrenergic bronchodilator.

Large doses of intravenous albuterol have been reported to aggravate pre-existing diabetes mellitus and ketoacidosis. As with other beta-agonists, albuterol may produce significant hypokalemia in some patients, possibly through intracellular shunting, which has the potential to produce adverse cardiovascular effects. The decrease is usually transient, not requiring supplementation.

Information For Patients

The action of Albuterol Inhalation Aerosol may last up to 6 hours or longer. Albuterol Inhalation Aerosol should not be used more frequently than recommended. Do not increase the dose or frequency of doses of Albuterol Inhalation Aerosol without consulting your physician. If you find that treatment with Albuterol Inhalation Aerosol becomes less effective for symptomatic relief, your symptoms become worse, and/or you need to use the product more frequently than usual, you should seek medical attention immediately. While you are using Albuterol Inhalation Aerosol, other inhaled drugs and asthma medications should be taken only as directed by your physician. Common adverse effects include palpitations, chest pain, rapid heart rate, tremor, or nervousness. If you are pregnant or nursing, contact your physician about the use of Albuterol Inhalation Aerosol. Effective and safe use of Albuterol Inhalation Aerosol includes an understanding of the way that it should be administered. See Illustrated Patient's Instructions For Use.

The contents of Albuterol Inhalation Aerosol are under pressure. Do not puncture. Do not use or store near heat or open flame. Exposure to temperatures above 120°F may cause bursting. Never throw container into fire or incinerator. Keep out of reach of children. Avoid spraying in eyes.

Drug Interactions

Other short-acting sympathomimetic aerosol bronchodilators should not be used concomitantly with albuterol. If additional adrenergic drugs are to be administered by any route, they should be used with caution to avoid deleterious cardiovascular effects.

Beta Blockers

Beta-adrenergic receptor blocking agents not only block the pulmonary effect of beta-agonists, such as Albuterol Inhalation Aerosol but may produce severe bronchospasm in asthmatic patients. Therefore, patients with asthma should not normally be treated with beta-blockers. However, under certain circumstances, eg, as prophylaxis after myocardial infarction, there may be no acceptable alternatives to the use of beta-adrenergic blocking agents in patients with asthma. In this setting, cardioselective beta-blockers could be considered, although they should be administered with caution.

Diuretics

The ECG changes and/or hypokalemia that may result from the administration of nonpotassium-sparing diuretics (such as loop or thiazide diuretics) can be acutely worsened by beta-agonists, especially when the recommended dose of the beta-agonist is exceeded. Although the clinical significance of these effects is not known, caution is advised in the coadministration of beta-agonists with nonpotassium-sparing diuretics.

Digoxin

Mean decreases of 16% to 22% in serum digoxin levels were demonstrated after single dose intravenous and oral administration of albuterol, respectively, to normal volunteers who had received digoxin for 10 days. The clinical significance of this finding for patients with obstructive airway disease who are receiving albuterol and digoxin on a chronic basis is unclear. Nevertheless, it would be prudent to carefully evaluate the serum digoxin levels in patients who are currently receiving digoxin and albuterol.

Monoamine Oxidase Inhibitors or Tricyclic Antidepressants

Albuterol should be administered with extreme caution to patients being treated with monoamine oxidase inhibitors or tricyclic antidepressants, or within 2 weeks of discontinuation of such agents, because the action of albuterol on the vascular system may be potentiated.

Carcinogenesis, Mutagenesis, and Impairment of Fertility

In a 2-year study in Sprague-Dawley rats, albuterol sulfate caused a significant dose-related increase in the incidence of benign leiomyomas of the mesovarium at and above dietary doses of 2.0 mg/kg (approximately 15 times the maximum recommended daily inhalation dose for adults on a mg/m^2 basis). In another study this effect was blocked by the coadministration of propranolol, a non-selective beta-adrenergic antagonist.

In an 18-month study in CD-1 mice, albuterol sulfate showed no evidence of tumorigenicity at dietary doses up to 500 mg/kg (approximately 1700 times the maximum recommended daily inhalation dose for adults on a mg/m^2 basis). In a 22-month study in the Golden Hamster, albuterol sulfate showed no evidence of tumorigenicity at dietary doses up to 50 mg/kg (approximately 230 times the maximum recommended daily inhalation dose for adults on a mg/m^2 basis).

Albuterol sulfate was not mutagenic in the Ames test with or without metabolic activation using tester strains S. typhimurium TA1537, TA1538, and TA98 or E. coli WP2, WP2uvrA, and WP67. No forward mutation was seen in yeast strain S. cerevisiae S9 nor any mitotic gene conversion in yeast strain S. cerevisiae JD1 with or without metabolic activation. Fluctuation assays in S. typhimurium TA98 and E. coli WP2, both with metabolic activation, were negative. Albuterol sulfate was not clastogenic in a human peripheral lymphocyte assay or in an AH1 strain mouse micronucleus assay.

Reproduction studies in rats demonstrated no evidence of impaired fertility at oral doses of albuterol sulfate up to 50 mg/kg (approximately 340 times the maximum recommended daily inhalation dose for adults on a mg/m^2 basis).

Teratogenic Effects—Pregnancy Category C

Albuterol sulfate has been shown to be teratogenic in mice. A study in CD-1 mice at subcutaneous (sc) doses at and above 0.25 mg/kg (approximately equal to the maximum recommended daily inhalation dose for adults on a mg/m^2 basis), induced cleft palate formation in 5 of 111 (4.5%) fetuses. At an sc dose of 2.5 mg/kg (approximately 8 times the maximum recommended daily inhalation dose for adults on a mg/m^2 basis) albuterol sulfate induced cleft palate formation in 10 of 108 (9.3%) fetuses. The drug did not induce cleft palate formation when administered at an sc dose of 0.025 mg/kg (significantly less than the maximum recommended daily inhalation dose for adults on a mg/m^2 basis). Cleft palate also occurred in 22 of 72 (30.5%) fetuses from females treated with 2.5 mg/kg isoproterenol (positive control) administered subcutaneously.

A reproduction study in Stride Dutch rabbits revealed cranioschisis in 7 of 19 (37%) fetuses when albuterol sulfate was administered orally at a dose of 50 mg/kg (approximately 680 times the maximum recommended daily inhalation dose for adults on a mg/m^2 basis).

Studies in pregnant rats with tritiated albuterol demonstrated that approximately 10% of the circulating maternal drug is transferred to the fetus. Disposition in the fetal lungs is comparable to maternal lungs, but fetal liver disposition is 1% of the maternal liver levels.

There are no adequate and well-controlled studies in pregnant women. Because animal reproduction studies are not always predictive of human response, albuterol should be used during pregnancy only if the potential benefit justifies the potential risk to the fetus.

During worldwide marketing experience, various congenital anomalies, including cleft palate and limb defects, have been reported in the offspring of patients being treated with albuterol. Some of the mothers were taking multiple medications during their pregnancies. Because no consistent pattern of defects can be discerned, a relationship between albuterol use and congenital anomalies has not been established.

Use in Labor and Delivery—Use in Labor

Because of the potential for beta-agonist interference with uterine contractility, use of Albuterol Inhalation Aerosol for relief of bronchospasm during labor should be restricted to those patients in whom the benefits clearly outweigh the risk.

Tocolysis

Albuterol has not been approved for the management of preterm labor. The benefit:risk ratio when albuterol is administered for tocolysis has not been established. Serious adverse reactions, including maternal pulmonary edema, have been reported during or following treatment of premature labor with beta2-agonists, including albuterol.

Nursing Mothers

It is not known whether this drug is excreted in human milk. Because of the potential for tumorigenicity shown for albuterol in some animal studies, a decision should be made whether to discontinue nursing or to discontinue the drug, taking into account the importance of the drug to the mother.

Pediatric Use

Safety and effectiveness in children below the age of 12 years have not been established.

ADVERSE REACTIONS

The adverse reactions of albuterol are similar in nature to those of other sympathomimetic agents, although the incidence of certain cardiovascular effects is less with albuterol.

Percent Incidence of Adverse Reactions in Patients ≥ 12 Years of Age in a 13-Week Clinical Trial [A 13-week double-blind study compared albuterol and isoproterenol aerosols in 147 asthmatic patients.] (n=147)
Adverse Event | Albuterol Inhalation Aerosol | Isoproterenol Inhaler
Tremor | < 15 | < 15
Nausea | < 15 | < 15
Tachycardia | 10 | 10
Palpitations | < 10 | < 15
Nervousness | < 10 | < 15
Increased Blood Pressure | < 5 | < 5
Dizziness | < 5 | < 5
Heartburn | < 5 | < 5

Cases of urticaria, angioedema, rash, bronchospasm, hoarseness, oropharyngeal edema, and arrhythmias (including atrial fibrillation, supraventricular tachycardia, and extrasystoles) have also been reported after the use of inhaled albuterol. In addition, albuterol, like other sympathomimetic agents, can cause adverse reactions such as hypertension, angina, vomiting, vertigo, central nervous system stimulation, insomnia, headache, unusual taste, and drying or irritation of the oropharynx.

OVERDOSAGE

The expected symptoms with overdosage are those of excessive beta-adrenergic stimulation and/or occurrence or exaggeration of any of the symptoms listed under ADVERSE REACTIONS, eg, angina, hypertension, tachycardia with rates up to 200 beats per minute, nervousness, headache, tremor, dry mouth, palpitation, nausea, dizziness, and insomnia. In addition, seizures, hypotension, arrhythmias, fatigue, malaise, and hypokalemia may also occur. As with all sympathomimetic aerosol medications, cardiac arrest and even death may be associated with abuse of Albuterol Inhalation Aerosol. Treatment consists of discontinuation of Albuterol Inhalation Aerosol together with appropriate symptomatic therapy. The judicious use of a cardioselective beta-receptor blocker may be considered, bearing in mind that such medication can produce bronchospasm. There is insufficient evidence to determine if dialysis is beneficial for overdosage of Albuterol Inhalation Aerosol.

The oral median lethal dose of albuterol sulfate in mice is greater than 2000 mg/kg (approximately 6800 times the maximum recommended daily inhalation dose for adults on a mg/m^2 basis). In mature rats, the subcutaneous median lethal dose of albuterol sulfate is approximately 450 mg/kg (approximately 3000 times the maximum recommended daily inhalation dose for adults on a mg/m^2 basis). In small young rats, the subcutaneous median lethal dose is approximately 2000 mg/kg (approximately 14,000 times the maximum recommended daily inhalation dose for adults and children on a mg/m^2 basis). The inhalation median lethal dose has not been determined in animals.

DOSAGE AND ADMINISTRATION

Treatment of acute episodes of bronchospasm or prevention of asthmatic symptoms

The usual dosage for adults and children 12 years of age and older is 2 inhalations repeated every 4 to 6 hours; in some patients, 1 inhalation every 4 hours may be sufficient. More frequent administration or a larger number of inhalations is not recommended. For maintenance therapy or prevention of exacerbation of bronchospasm, 2 inhalations, 4 times a day should be sufficient.

The use of Albuterol Inhalation Aerosol can be continued as medically indicated to control recurring bouts of bronchospasm. During this time most patients gain optimal benefit from regular use of the inhaler. Safe usage for periods extending over several years has been documented.

If a previously effective dosage regimen fails to provide the usual response, this may be a marker of destabilization of asthma and requires re-evaluation of the patient and treatment regimen, giving special consideration to the possible need for anti-inflammatory treatment, eg, corticosteroids.

Exercise-Induced Bronchospasm Prevention

The usual dosage for adults and children 12 years and older is 2 inhalations, 15 minutes prior to exercise. For treatment, see above.

As with all other inhalation aerosol medications, patients should make sure that the canister is firmly seated in the plastic mouthpiece before each use and the product is primed at specific times. Patients should prime Albuterol Inhalation Aerosol by actuating into the air, away from the eyes and face, four times before using for the first time and two times when the aerosol has not been used for a period of at least four days.

HOW SUPPLIED

Albuterol Inhalation Aerosol, 17.0 g canister contains 200 metered inhalations, box of one (NDC 59930-1560-1). Each actuation delivers 100 mcg of albuterol from the valve and 90 mcg of albuterol from the mouthpiece. Each canister is supplied with a white plastic actuator with white dust cap, and Patient's Instructions.

Albuterol Inhalation Aerosol REFILL canister, 17.0 g, contains 200 metered inhalations, with Patient's Instructions; box of one (NDC 59930-1560-2).

The correct amount of medication in each inhalation cannot be assured after 200 actuations from the 17.0 g canister or 80 actuations from the 6.8 g canister even though the canister is not completely empty. The canister should be discarded when the labeled number of actuations have been used.

Store at 25°C (77°F); excursions permitted to 15–30°C (59–86°F) [see USP Controlled Room Temperature]. Failure to use the product within this temperature range may result in improper dosing. For optimal results, the canister should be at room temperature before use. Shake well before using.

Albuterol Inhalation Aerosol canister should be used only with the actuator provided. The white actuator should not be used with other aerosol medication canisters.

Note: The indented statement below is required by the Federal government's Clean Air Act for all products containing or manufactured with chlorofluorocarbons (CFCs).

WARNING: Contains dichlorodifluoromethane (CFC-12) and trichloromonofluoromethane (CFC-11), substances which harm public health and the environment by destroying ozone in the upper atmosphere.

A notice similar to the above WARNING has been placed in the "Patient's Instructions for Use" portion of this package insert under the Environmental Protection Agency's (EPA's) regulations. The patient's warning states that the patient should consult his or her physician if there are questions about alternatives.

Warrick Pharmaceuticals Corporation
Reno, NV 89506 USA

Rev. 5/04
B-19529550
2194

Copyright © 1994, 1999, Warrick Pharmaceuticals Corporation.
All rights reserved.

SUPPLEMENTAL PATIENT MATERIAL

Albuterol, USP Inhalation Aerosol

Patient's Instructions For Use

Figure 1 Figure 2

Figure 3

Before using your Albuterol Inhalation Aerosol, read complete instructions carefully.

1. SHAKE THE INHALER WELL immediately before each use. Then remove the cap from the mouthpiece. Check mouthpiece for foreign objects prior to use. Make sure the canister is fully and firmly inserted into the actuator. The Albuterol Inhalation Aerosol canister should only be used with the white Albuterol Inhalation Aerosol mouthpiece. This white mouthpiece should not be used with any other inhalation drug product. Similarly, the canister should not be used with other mouthpieces.
2. As with all other inhalation aerosol medications, patients should make sure that the canister is firmly seated in the plastic mouthpiece adapter before each use and the product is primed at specific times. Patients should prime Albuterol Inhalation Aerosol by actuating into the air, away from the eyes and face, four times before using for the first time and two times when the aerosol has not been used for a period of at least four days.
3. BREATHE OUT FULLY THROUGH THE MOUTH, expelling as much air from your lungs as possible. Place the mouthpiece fully into the mouth, holding the inhaler in its upright position (See Figure 1) and closing the lips around it.
4. WHILE BREATHING IN DEEPLY AND SLOWLY THROUGH THE MOUTH, FULLY DEPRESS THE TOP OF THE METAL CANISTER with your index finger. (See Figure 2.)
5. HOLD YOUR BREATH AS LONG AS POSSIBLE. Before breathing out, remove the inhaler from your mouth and release your finger from the canister.
6. Wait one minute and SHAKE the inhaler again. Repeat steps 2 through 4 for each inhalation prescribed by your physician.
7. CLEANSE THE INHALER THOROUGHLY AND FREQUENTLY. Remove the metal canister and cleanse the plastic case and cap by rinsing thoroughly in warm running water, at least once a day. After thoroughly drying the plastic case and cap, gently replace the canister downward into the case without using a twisting motion. (See Figure 3.) Replace the cap.

DOSAGE: Use only as directed by your physician.

The correct amount of medication in each inhalation cannot be assured after 200 actuations from the 17.0 g canister or 80 actuations from the 6.8 g canister even though the canister is not completely empty. The canister should be discarded when the labeled number of actuations have been used. Before you reach the specified number of actuations, you should consult your physician to determine whether a refill is needed. Just as you should not take extra doses without consulting your physician, you also should not stop using Albuterol Inhalation Aerosol without consulting your physician.

WARNINGS: The action of Albuterol Inhalation Aerosol may last up to 6 hours or longer. Albuterol Inhalation Aerosol should not be used more frequently than recommended. Do not increase the dose or frequency of Albuterol Inhalation Aerosol without consulting your physician. If you find that treatment with Albuterol Inhalation Aerosol becomes less effective for symptomatic relief, your symptoms become worse, and/or you need to use the product more frequently than usual, you should seek immediate medical attention. While taking Albuterol Inhalation Aerosol, other asthma drugs and inhaled medicines should be used only as prescribed by your physician.

Contents Under Pressure. Do not puncture. Do not store near heat or open flame. Exposure to temperatures above 120°F may cause bursting. Never throw container into fire or incinerator. Keep out of reach of children. Avoid spraying in eyes.

Store at 25°C (77°F); excursions permitted to 15–30°C (59–86°F) [see USP Controlled Room Temperature]. Failure to use the product within this temperature range may result in improper dosing. Shake well before using. For optimal results, the canister should be at room temperature before use.

Note: The indented statement below is required by the Federal government's Clean Air Act for all products containing or manufactured with chlorofluorocarbons (CFCs).

This product contains dichlorodifluoromethane (CFC-12) and trichloromonofluoromethane (CFC-11), substances which harm the environment by destroying ozone in the upper atmosphere.

Your physician has determined that this product is likely to help your personal health. USE THIS PRODUCT AS DIRECTED, UNLESS INSTRUCTED TO DO OTHERWISE BY YOUR PHYSICIAN. If you have any questions about alternatives, consult with your physician.

Warrick Pharmaceuticals Corporation
Reno, NV 89506 USA

Copyright © 1994, 1999,
Warrick Pharmaceuticals Corporation.
All rights reserved.

19529550
Rev. 5/04